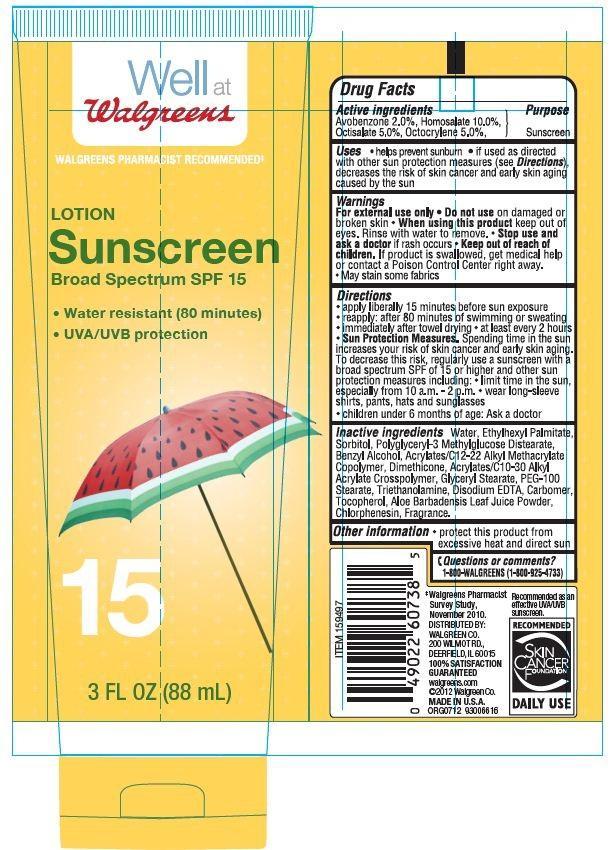 DRUG LABEL: Walgreens sunscreen
NDC: 0363-4013 | Form: LOTION
Manufacturer: WALGREEN CO.
Category: otc | Type: HUMAN OTC DRUG LABEL
Date: 20130807

ACTIVE INGREDIENTS: AVOBENZONE 2 g/100 g; HOMOSALATE 10 g/100 g; OCTISALATE 5 g/100 g; OCTOCRYLENE 5 g/100 g
INACTIVE INGREDIENTS: WATER; ETHYLHEXYL PALMITATE; SORBITOL; DIMETHICONE; TROLAMINE; GLYCERYL MONOSTEARATE; EDETATE DISODIUM; PEG-100 STEARATE; TOCOPHEROL; ALOE VERA LEAF; BENZYL ALCOHOL; CHLORPHENESIN

Drug Facts

Active ingredients

Avobenzone 2.0%

Homosalate 10.0%

Octisalate 5.0%

Octocrylene 5.0%

Purpose

Sunscreen

Uses

- helps prevent sunburn
- if used as directed with other sun protection measures (see Directions) decrease the risk of skin cancer and early skin aging caused by the sun.

Warnings

For external use only

When using this product

- keep out of eyes. Rinse with water to remove.

Stop use and ask a doctor if

rash occurs

Keep out of the reach of children.

If swallowed get medical help or contact a Poison Control Center right away.

May stain some fabrics

Directions

- apply liberally 15 minutes before sun exposure
- reapply: after 80 minutes of swimming or sweating
- immediately after towel drying
- at least every 2 hours

Sun protection measures.

Spending time in the sun increase your risk of skin cancer and early skin

aging. To decrease this risk regularly use a sunscreen with a broad spectrum SPF of 15 or higher and other sun protection measures including:

- Limit time in the sun, especially from 10 am - 2 pm
- Wear long sleeves shirts, pants, hats and sunglasses
- children under 6 month of age: Ask a doctor

Other information

protect this product from excessive heat and direct sun

Inactive ingredients

Water, Ethylhexyl Plamitate, Sorbitol, Polyglyceryl-3 Methylglucose Distearate, Acrylates/C12-22 Alkyl Methacrylate Copolymer, Acrylates/C10-30 Alkyl Acrylate Crosspolymer, Triethanolamine, Glyceryl Stearate, PEG_100 Stearate,Disodium EDTA, Oleth-3, Tocopherol,Aloe Barbadensis Leaf juice Powder,Benzyl Alcohol, Chlorphenesin, Fragrance.

Principal Display Panel

Well at

Walgreens

WALGREENS PHARMACY RECOMMENDED

LOTION

Sunscreen

Broad Spectrum SPF 15

Water resistant (80 minutes)

UVA/UVB protection

3 FL OZ (88 mL)